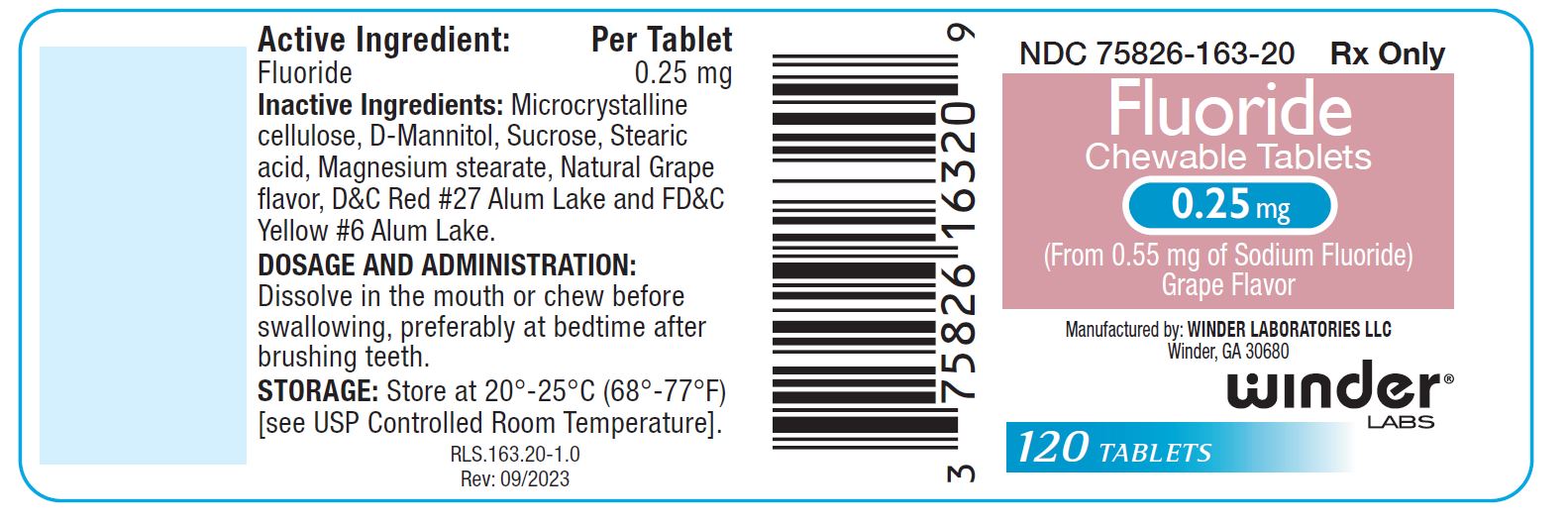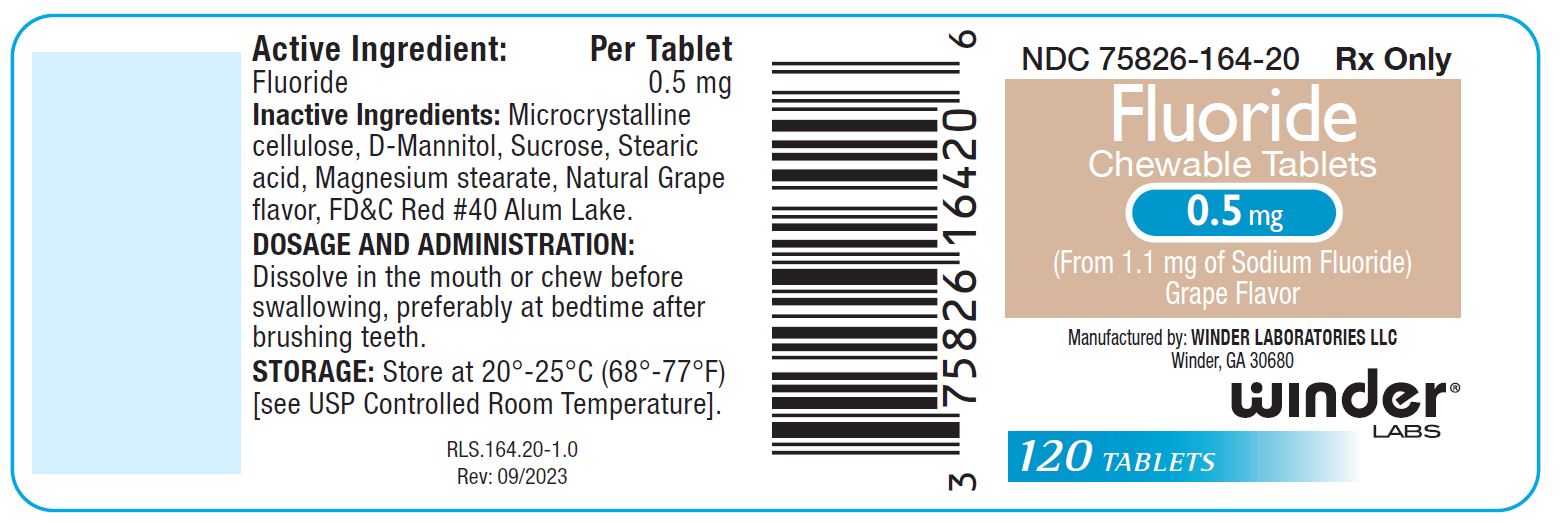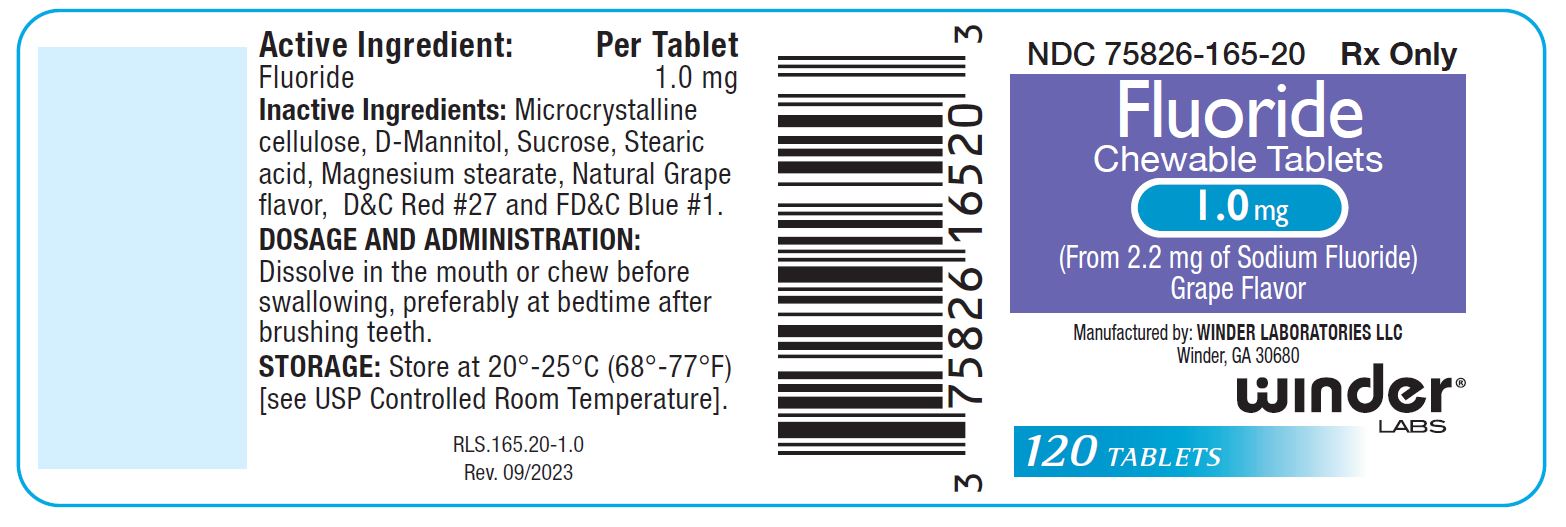 DRUG LABEL: Fluoride
NDC: 75826-163 | Form: TABLET, CHEWABLE
Manufacturer: WINDER LABORATORIES, LLC
Category: prescription | Type: HUMAN PRESCRIPTION DRUG LABEL
Date: 20260105

ACTIVE INGREDIENTS: SODIUM FLUORIDE 0.25 mg/1 1
INACTIVE INGREDIENTS: MICROCRYSTALLINE CELLULOSE 102; SUCROSE; MANNITOL; MAGNESIUM STEARATE; STEARIC ACID; FD&C YELLOW NO. 6; D&C RED NO. 27 ALUMINUM LAKE

FLUORIDE (sodium fluoride) tablet, chewable

Sodium Fluoride Chewable Tablets

This insert is for 1.0 mg strength tablets, 0.5 mg strength tablets, and 0.25 mg strength tablets.

Rx Only

This product is a prescription product for the clinical dietary management of the metabolic processes of caries prophylaxis.

120 Tablets per bottle

Water F¯ Content
Ages | 0 ppm F¯ to <0.3 ppm F¯ | 0.3 ppm F¯ to 0.6ppm F¯ | >0.6ppm F¯
3 yrs. to 6 yrs. | 0.5mg* | 0.25mg* | 0
>6yrs. to 16 yrs. | 1.0mg* | 0.5mg* | 0

* Per day

Active Ingredient:Fluoride (as Sodium Fluoride)

0.25 mg / 0.5 mg / 1.0 mg

Inactive Ingredients: Microcrystalline cellulose, D-Mannitol, Sucrose, Stearic acid, Magnesium stearate, Natural Grape flavor.

0.25mg also contains: D&C Red #27 Alum Lake and FD&C Yellow #6 Alum Lake.

0.5 mg also contains: FD&C Red #40 Alum Lake.

1.0 mg also contains: D&C Red #27 and FD&C Blue #1.

CLINICAL PHARMACOLOGY

Sodium Fluoride acts systemically (before tooth eruption) and topically (post-eruption) by increasing tooth resistance to acid dissolution, by promoting remineralization, and by inhibiting the cariogenic microbial process.

INDICATIONS AND USAGE

For once daily self-applied systemic use as a dental caries preventive in pediatric patients. It has been established that ingestion of fluoridated drinking water (1 ppm F¯) during the period of tooth development results in a significant decrease in the incidence of dental caries. Sodium Fluoride Chewable Tablets were developed to provide systemic fluoride for use as a supplement in pediatric patients from age 3 years to age 16 years and older living in areas where the drinking water fluoride contents does not exceed 0.6 ppm F¯.

CONTRAINDICATIONS

Fluoride 1.0 mg Tablets are contraindicated when the fluoride content of drinking water is >0.3 ppm F¯ and should not be administered to pediatric patients under 6 years.

Fluoride 0.5 mg Tablets are contraindicated when the fluoride content of drinking water is more than 0.6 ppm F¯ and should not be administered to pediatric patients under age 6 when the fluoride content of drinking water is 0.3 ppm F¯ or more or to pediatric patients under age 3 years.

Fluoride 0.25 mg Tablets are contraindicated when the fluoride content of drinking water is more than 0.6 ppm F¯ and should not be administered to pediatric patients under age 3 years when the fluoride content of drinking water is 0.3 ppm F¯ or more. Do not administer Sodium Fluoride Chewable Tablets (any strength) to pediatric patients under age 3 years. Sodium Fluoride Chewable Tablets (any strength) are not indicated for use in adults.

OVERDOSAGE

Accidental ingestion of large amounts of fluoride may result in acute burning in the mouth and sore tongue. Nausea, vomiting, and diarrhea may occur soon after ingestion (within 30 minutes) and are accompanied by salivation, hematemesis, and epigastric cramping abdominal pain. These symptoms may persist for 24 hours. If less than 5 mg fluoride/kg body weight (i.e., less than 2.3 mg fluoride/lb body weight) have been ingested, give calcium (e.g., milk) orally to relieve gastrointestinal symptoms and observe for a few hours. If more than 5 mg fluoride/kg body weight (i.e., more than 2.3 mg fluoride/lb body weight) have been ingested, induce vomiting, give orally soluble calcium (e.g., milk, 5% calcium gluconate or calcium lactate solution) and immediately seek medical assistance. For accidental ingestion of more than 15 mg fluoride/kg body weight (i.e., more than 6.9 mg fluoride/lb body weight), induce vomiting and admit immediately to a hospital facility.

A bottle of 120 0.25 mg tablets contains 30 mg fluoride. A bottle of 120 0.5 mg tablets contains 60 mg fluoride. A bottle of 120 1 mg tablets contains 120 mg fluoride. [The total amount of sodium fluoride in a bottle of 120 Fluoride Chewable Tablets (all strengths) conforms with the recommended amount of the American Dental Association for the maximum to be dispensed at one time for safety purposes.]

WARNING

Prolonged daily ingestion of quantities greater than the recommended amount may result in various degrees of dental fluorosis in pediatric patients under age 6 years, especially if the water fluoridation exceeds 0.6 ppm. Read directions carefully before using. This product, as all chewable tablets, is not recommended for children under age 3 due to risk of choking.

Keep out of the reach of infants and children.

PRECAUTIONS

General

Please refer to the CONTRAINDICATIONS, WARNINGSand OVERDOSAGEsections for overdosage concerns. Use in pediatric patients below the age of 3 years is not recommended by current American Dental Associations and American Academy of Pediatrics guidelines.

Drug Interactions:

Do not eat or drink dairy products within one hour of fluoride administration. Incompatibility of fluoride with dairy foods has been reported due to formation of calcium fluoride which is poorly absorbed.

Carcinogenesis, Mutagenesis, Impairment of Fertility

In a study conducted in rodents, no carcinogenesis was found in male and female rats treated with fluoride at dose levels ranging from 4.1 to 9.1 mg/kg of body weight. Equivocal evidence of carcinogenesis was reported for male rats treated with 2.5 and 4.1 mg/kg of body weight. In a second study, no carcinogenesis was observed in rats, males or females, treated with fluoride up to 11.3 mg/kg of body weight. This dose is at least 400 times greater than the recommended daily dose of Sodium Fluoride Chewable Tablets. Fluoride ion is not mutagenic in standard bacterial systems. It has been shown that fluoride ion has potential to induce chromosome aberrations in cultured human and rodentcells at does much higher than those to which humans are exposed. In vivo data is conflicting. Some studies report chromosome damage in rodents while other studies using similar protocols report negative results. Potential adverse reproductive effects of fluoride exposure in humans has not been adequately evaluated. Adverse effects on reproduction were reported for rats, mice, fox, and cattle exposed to 100 ppm or greater concentrations of fluoride in their diet or drinking water. Other studies conducted in rats demonstrated that lower doses of fluoride (5 mg/kg of body weight) did not result in impaired fertility and reproductive capabilities. This dose is approximately 200 times greater than the recommended daily dose of Sodium Fluoride Chewable Tablets.

Pregnancy

Teratogenic Effects

Pregnancy Category B

It has been shown that fluoride crosses the placenta of rats, but only 0.01% of the amount administered is incorporated in fetal tissue. Animal studies (rats, mice, rabbits) have shown that fluoride is not a teratogen. Maternal exposure to 12.2 mg fluoride/kg of body weight (rats) or 13.1 mg/kg of body weight (rabbits) did not affect the litter size or fetal weight and did not increase the frequency of skeletal or visceral malformations. Epidemiological studies conducted in areas with high levels of naturally fluoridated water showed no increase in birth defects. Heavy exposure to fluoride during in utero development may result in skeletal fluorosis which becomes evident in childhood.

Nursing Mothers

It is not known if fluoride is excreted in human milk. However, many drugs are excreted in human milk and caution should be exercised when Sodium Fluoride Chewable Tablets are administered to a nursing woman. Reduced milk production was reported in farm raised fox when the animals were fed a diet containing a high concentration of fluoride (98-137 mg/kg of body weight). No adverse effects on parturition, lactation, or offspring were seen in rats administered fluoride up to 5 mg/kg of body weight. This dose is at least 200 times greater than the recommended daily dose of Sodium Fluoride Chewable Tablets.

Geriatric Use

Sodium Fluoride Chewable Tablets (any strength) are not indicated for use in geriatric patients.

Pediatric Use

The use of Sodium Fluoride Chewable Tablets as a caries preventive in pediatric age groups 3 years to 16 years is supported by evidence from adequate and well controlled studies on fluoride supplementation from birth through adolescence.

ADVERSE REACTIONS

Allergic rash and other idiosyncrasies have been rarely reported.

Call your doctor for medical advice about side effects.
You may report side effects to the FDA at 1(800) FDA-1088.

DOSAGE AND ADMINISTRATION

(for dosage see table)

Dissolve in the mouth or chew before swallowing, preferably at bedtime after brushing teeth. See schedule below to determine dosage.

HOW SUPPLIED

120 count Chewable tablets

Each tablet contains 0.25 mg Fluoride from 0.55 mg Sodium Fluoride. Pink-colored, grape flavor, un-scored, round chewable tablet, debossed with "WL" "163" on one side and plain on other side of tablet. NDC 75826-163-20 (120 count).

Each tablet contains 0.5 mg Fluoride from 1.1 mg Sodium Fluoride. Peach-colored, grape flavor, un-scored, round chewable tablet, debossed with “WL" "164” on one side and plain on other side of tablet. NDC 75826-164-20 (120 count).

Each tablet contains 1.0 mg Fluoride from 2.2 mg Sodium Fluoride. Purple-colored, grape flavor, un-scored, round chewable tablet, debossed with “WL” “165” on one side and plain on other side of tablet. NDC 75826-165-20 (120 count).

STORAGE

Store at 25° C (77° F); excursions permitted to 15° - 30° C (59° - 86° F). See USP Controlled Room Temperature. Protect from light and moisture.

Dispense in a tight, light-resistant container with a child-resistant closure as defined in the USP/NF.

Warning: Keep this and all medications out of the reach of children. In case of accidental overdose, seek professional assistance or contact a poison control center immediately.

REFERENCES

Manufactured by:
Winder Laboratories LLC
Winder GA, 30680

RLS.164.99-1.0

Rev: 09/2023